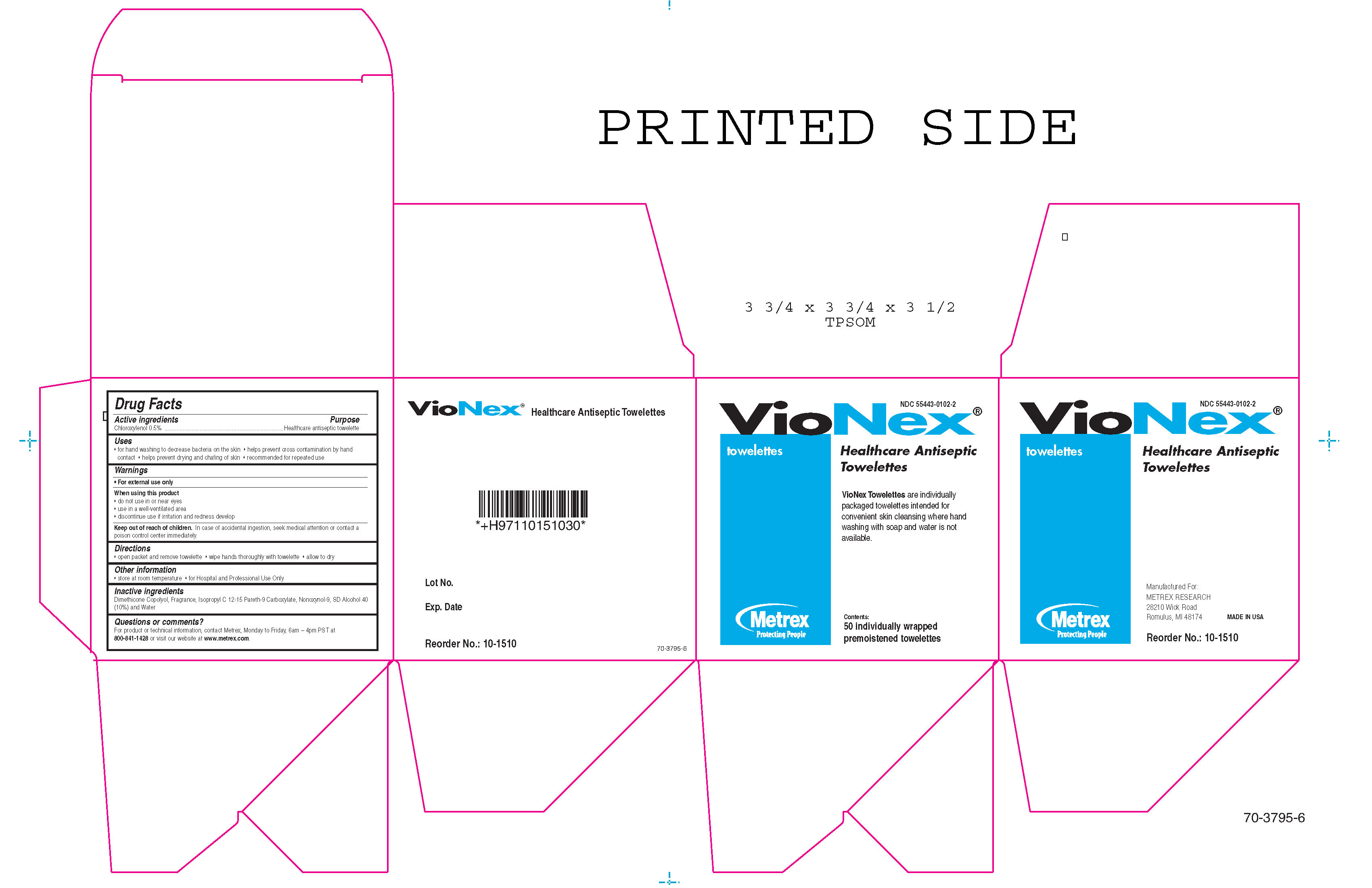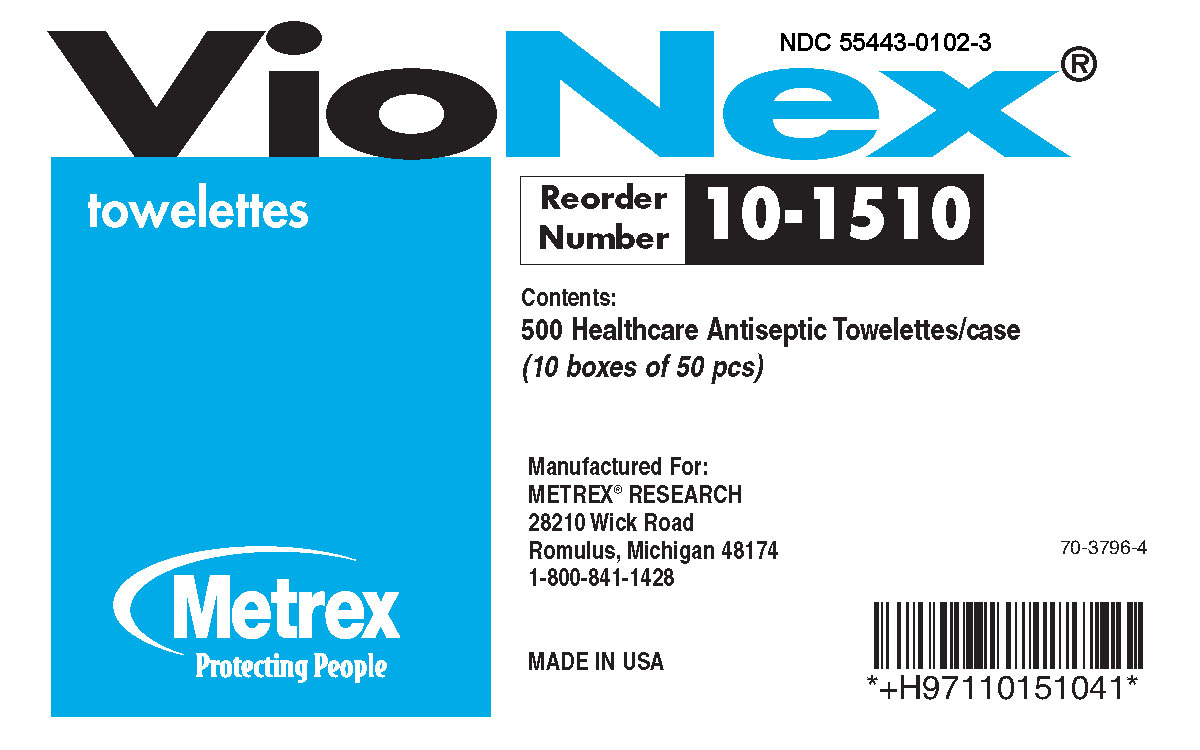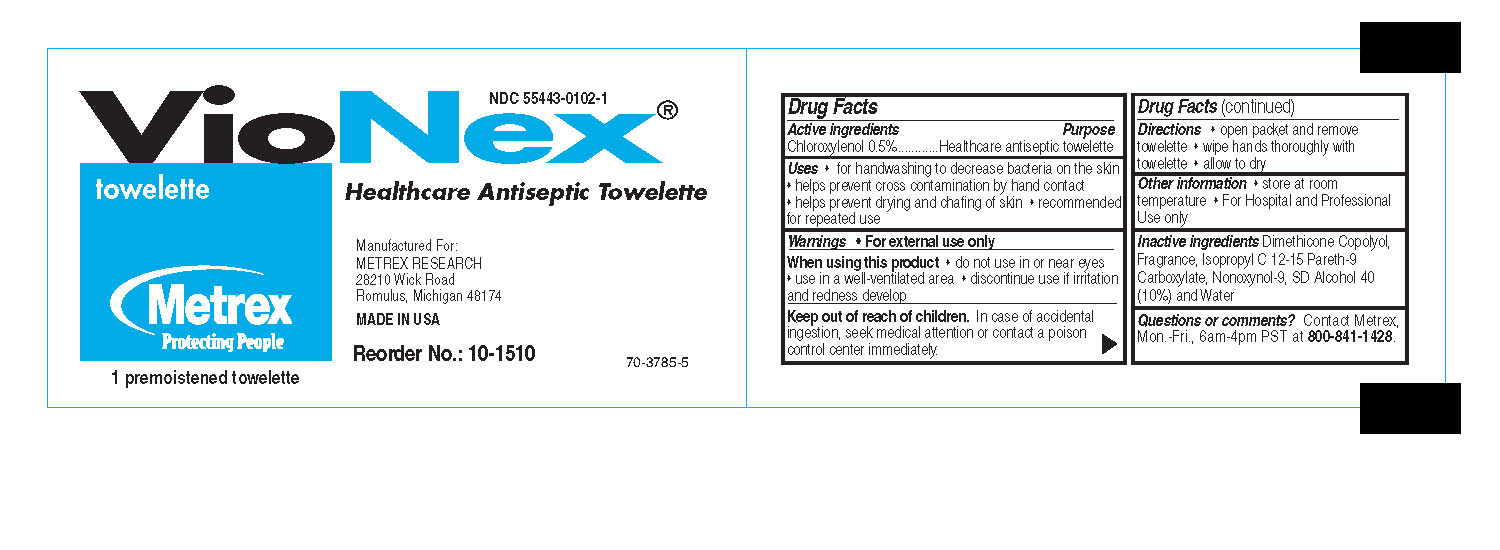 DRUG LABEL: VioNex Towelette
NDC: 55443-0102 | Form: CLOTH
Manufacturer: Metrex Research
Category: otc | Type: HUMAN OTC DRUG LABEL
Date: 20100218

ACTIVE INGREDIENTS: Chloroxylenol 0.5 g/100 g

VioNex Towelette

Drug Facts

Active ingredients Purpose
Chloroxylenol 0.5%............Healthcare antiseptic towelette

Uses

- for handwashing to decrease bacteria on the skin
- helps prevent cross contamination by hand contact
- helps prevent drying and chafing of skin
- recommended for repeated use

Warnings

- For external use only

When using this product

- do not use in or near eyes
- use in a well-ventilated area
- discontinue use if irritation and redness develop

Keep out of reach of children

In case of accidental ingestion, seek medical attention or contact a poison control center immediately.

Inactive Ingredients

Dimethicone Copolyol, Fragrance, Isopropyl C 12-15 Pareth-9 Carboxylate, Nonoxynol-9, SD Alcohol 40 (10%) and Water

Questions or comments?

Contact Metrex, Mon.-Fri., 6am-4pm PST at 800-841-1428

Directions

- open packet and remove towelette
- wipe hands thoroughly with towelette
- allow to dry

Other Information

- store at room temperature
- For Hospital and Professional Use only

PACKAGE LABEL

VioNex
towelette
Healthcare Antiseptic Towelette
VioNex Towelettes are individually packaged towelettes intended for convenient skin cleansing where hand washing with soap and water is not available.
Metrex
Protecting People
Manufactured For:
METREX RESEARCH CORPORATION
28210 Wick Road
Romulus, Michigan 48174
MADE IN USA
1 premoistened towelette
Contents: 50 individually wrapped premoistened towelettes

PACKAGE LABEL

Box Image

PACKAGE LABEL

Case Image